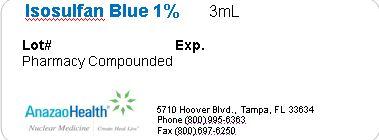 DRUG LABEL: Isosulfan Blue
NDC: 51808-206 | Form: SOLUTION
Manufacturer: AnazaoHealth Corporation
Category: prescription | Type: HUMAN PRESCRIPTION DRUG LABEL
Date: 20120619

ACTIVE INGREDIENTS: ISOSULFAN BLUE 10 mg/1 mL

Isosulfan Blue 1%

DESCRIPTION

Dear Medical Professional,

Per your order we have compounded Isosulfan Blue 1%. The characteristics of this compounded preparation are as follows:

CLINICAL PHARMACOLOGY

Isosulfan Blue has no known pharmacologic action. Following subcutaneous administration, Isosulfan blue 1% is selectively picked up by the lymphatic vessels. Thus, the lymphatic vessels are delineated by a bright blue color making them discernible from surrounding tissue. There is some evidence that 50% of the isosulfan blue, from aqueous solution, is weakly bound to serum protein (albumin). Since interstitial protein is presumed to be carried almost exclusively by lymphtics, and in view of evidence of binding of dyes to proteins, visualization may be due to protein binding phenomenon.

INDICATIONS AND USAGE

Isosulfan Blue 1% Injection delineates the lymphatic vessels following subcutaneous administration. It is an adjunct to lymphography (in primary and secondary lymphedema of the extremities; chyluria, chylous ascites or chylothorax; lymph node involvement by primary or secondary neoplasm; and lymph node response to therapeutic modalities) for visualization to the lymphatic system draining the region of injection

DOSAGE AND ADMINISTRATION

Isosulfan Blue 1% is to be administered subcutaneously, one-half (1/2) ml into three (3) interdigital spaces of each extremity per study. A maximum dose of 3 ml (30 mg) isosulfan blue is injected.

CONTRAINDICATIONS

Hypersensitivity to triphenylmethane or related compounds

PRECAUTIONS

After subcutaneous administration of Isosulfan blue 1%, competent personnel and emergency facilities should be available for at least 30-60 minutes, since severe delayed reactions have been known to occur with similar compounds.

The admixture of Isosulfan blue with local anesthetics (i.e. lidocaine) in the same syringe prior to administration resulted in an immediate precipitation of 4-9% of the drug complex. This technique is not recommended

ADVERSE REACTIONS

Isosulfan blue 1% has demonstrated a 1.5% incidence of adverse reactions. All the reactions were of an allergic type such as localized swelling at the site of administration and mild pruritis of hands, abdomen and neck have been reported within several minutes following administration of the drug.

Storage and Handling

Store at room temperature

PACKAGE LABEL.PRINCIPAL DISPLAY PANEL

Figure 1